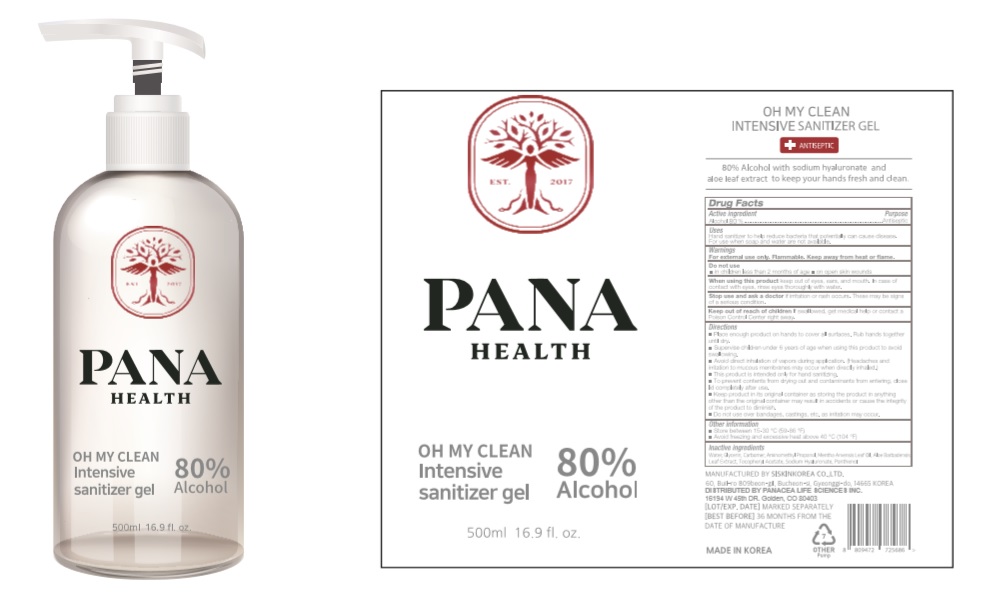 DRUG LABEL: OHMYCLEAN Intensive sanitizer gel
NDC: 74456-058 | Form: GEL
Manufacturer: Panacea Life Sciences
Category: otc | Type: HUMAN OTC DRUG LABEL
Date: 20200424

ACTIVE INGREDIENTS: ALCOHOL 400 mL/500 mL
INACTIVE INGREDIENTS: PANTHENOL; MENTHA ARVENSIS LEAF OIL; GLYCERIN; .ALPHA.-TOCOPHEROL ACETATE; ALOE VERA LEAF; WATER; AMINOMETHYL PROPANEDIOL; CARBOMER HOMOPOLYMER, UNSPECIFIED TYPE; HYALURONATE SODIUM

[Private label distributor-PANACEA LIFE SCIENCES] 500ml_80%_gel_OHMYCLEAN Intensive sanitizer gel[74456-058-01]